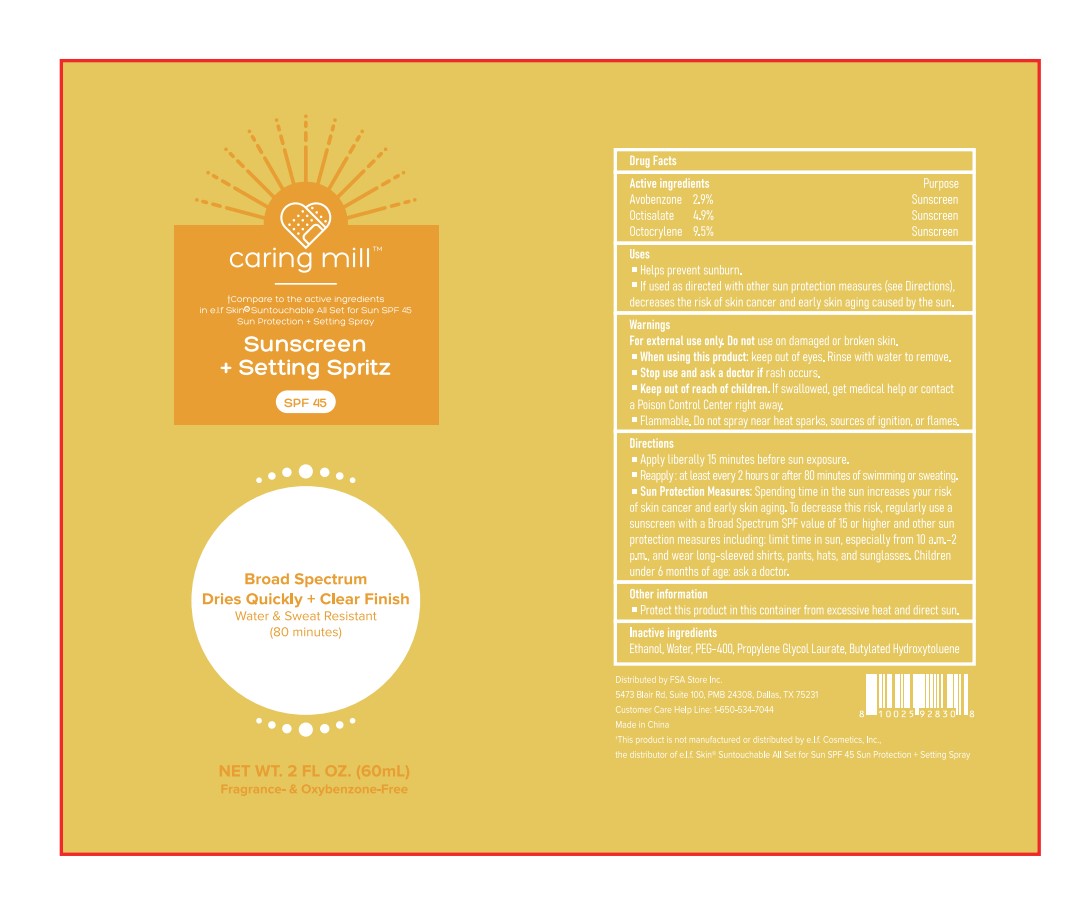 DRUG LABEL: Sunscreen Setting Spritz, SPF 45
NDC: 81522-228 | Form: SPRAY
Manufacturer: FSA Store Inc
Category: otc | Type: HUMAN OTC DRUG LABEL
Date: 20251231

ACTIVE INGREDIENTS: OCTISALATE 2.94 g/60 mL; AVOBENZONE 1.74 g/60 mL; OCTOCRYLENE 5.7 g/60 mL
INACTIVE INGREDIENTS: POLYETHYLENE GLYCOL 400; PROPYLENE GLYCOL LAURATE; AQUA; ALCOHOL; BHT

81522-228 Sunscreen Setting Spritz, SPF 45

ACTIVE INGREDIENT

AVOBENZONE G63QQF2NOX 2.9%
OCTISALATE 4X49Y0596W 4.9%
OCTOCRYLENE 5A68WGF6WM 9.5%

PURPOSE

Sunscreen

Keep out of reach of children.lf swallowed, get medical help or contacta Poison Control
Center right away
Flammable. Do not spray near heat sparks, sources of ignition, or flames

Warnings
For external use only Do not use on damaged or broken skin.
When using this product: keep out of eyes, Rinse with water to remove.
Stop use and ask a doctor if rash occurs.
Keep out of reach of children.lf swallowed, get medical help or contacta Poison Control
Center right away
Flammable. Do not spray near heat sparks, sources of ignition, or flames

Directions
Apply liberally 15 minutes before sun exposure. Reaooly. at least every 2 hours or after
80 minutes ofswimming or sweating.Sun Protection Measures, Spending time in the sun
increases your riskof skan cancer and early skin aging. lo decrease this risk, regularly
use asunscreen with a Broad Spectrum SPF value of 15 or higher and other
sunprotection measures including, limit time in sun, especiallv from 10 a.m.-2p.m, and
wear long-sleeved shirts, pants, hats, and sunalasses. Chitdrenunder 6 months of age:
ask a doctor.

DOSAGE AND ADMINISTRATION

Apply tiberally 15 minutes before sun exposure.
Reapoly. at least every 2 hours or after 80 minutes of swimming or sweating.

INACTIVE INGREDIENT

WATER
BHT
ALCOHOL
PEG-400
PROPYLENE GLYCOL LAURATE